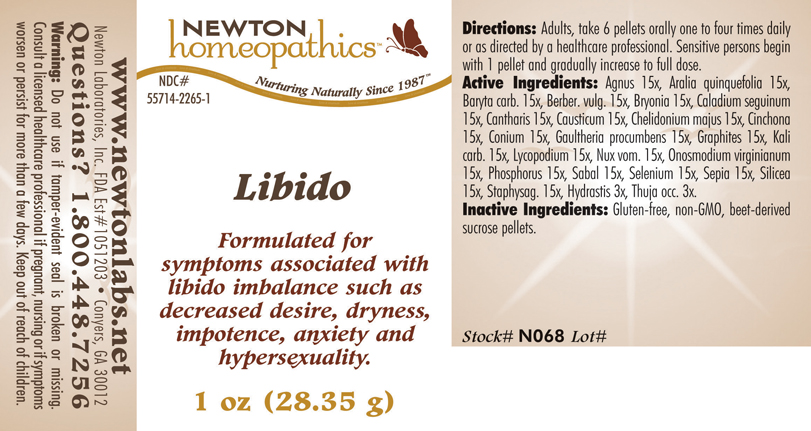 DRUG LABEL: Libido 
NDC: 55714-2265 | Form: PELLET
Manufacturer: Newton Laboratories, Inc.
Category: homeopathic | Type: HUMAN OTC DRUG LABEL
Date: 20110301

ACTIVE INGREDIENTS: Chaste Tree 15 [hp_X]/1 g; American Ginseng 15 [hp_X]/1 g; Barium Carbonate 15 [hp_X]/1 g; Berberis Vulgaris Root Bark 15 [hp_X]/1 g; Bryonia Alba Root 15 [hp_X]/1 g; Dieffenbachia Seguine 15 [hp_X]/1 g; Lytta Vesicatoria 15 [hp_X]/1 g; Causticum 15 [hp_X]/1 g; Chelidonium Majus 15 [hp_X]/1 g; Cinchona Officinalis Bark 15 [hp_X]/1 g; Conium Maculatum Flowering Top 15 [hp_X]/1 g; Gaultheria Procumbens Top 15 [hp_X]/1 g; Graphite 15 [hp_X]/1 g; Potassium Carbonate 15 [hp_X]/1 g; Lycopodium Clavatum Spore 15 [hp_X]/1 g; Strychnos Nux-vomica Seed 15 [hp_X]/1 g; Onosmodium Virginianum Whole 15 [hp_X]/1 g; Phosphorus 15 [hp_X]/1 g; Saw Palmetto 15 [hp_X]/1 g; Selenium 15 [hp_X]/1 g; Sepia Officinalis Juice 15 [hp_X]/1 g; Silicon Dioxide 15 [hp_X]/1 g; Delphinium Staphisagria Seed 15 [hp_X]/1 g; Goldenseal 3 [hp_X]/1 g; Thuja Occidentalis Leafy Twig 3 [hp_X]/1 g
INACTIVE INGREDIENTS: Sucrose

Libido

INDICATIONS & USAGE SECTION

Libido Formulated for symptoms associated with libido imbalance such as decreased desire, dryness, impotence, anxiety and hypersexuality.

DOSAGE & ADMINISTRATION SECTION

Directions: Adults, take 6 pellets orally one to four times daily or as directed by a healthcare professional. Sensitive persons begin with 1 pellet and gradually increase to full dose.

OTC - ACTIVE INGREDIENT SECTION

Agnus 15x, Aralia quinquefolia 15x, Baryta carb. 15x, Berber. vulg. 15x, Bryonia 15x, Caladium seguinum 15x, Cantharis 15x, Causticum 15x, Chelidonium majus 15x, Cinchona 15x, Conium 15x, Gaultheria procumbens 15x, Graphites 15x, Kali carb. 15x, Lycopodium 15x, Nux vom. 15x, Onosmodium virginianum 15x, Phosphorus 15x, Sabal 15x, Selenium 15x, Sepia 15x, Silicea 15x, Staphysag. 15x, Hydrastis 3x, Thuja occ. 3x.

OTC - PURPOSE SECTION

Formulated for symptoms associated with libido imbalance such as decreased desire, dryness, impotence, anxiety and hypersexuality.

INACTIVE INGREDIENT SECTION

Inactive Ingredients: Gluten-free, non-GMO, beet-derived sucrose pellets.

QUESTIONS SECTION

www.newtonlabs.net Newton Laboratories, Inc. FDA Est # 1051203 - Conyers, GA 30012
Questions? 1.800.448.7256

WARNINGS SECTION

Warning: Do not use if tamper - evident seal is broken or missing. Consult a licensed healthcare professional if pregnant, nursing or if symptoms worsen or persist for more than a few days. Keep out of reach of children.

OTC - PREGNANCY OR BREAST FEEDING SECTION

Consult a licensed healthcare professional if pregnant, nursing or if symptoms worsen or persist for more than a few days.

OTC - KEEP OUT OF REACH OF CHILDREN SECTION

Keep out of reach of children.